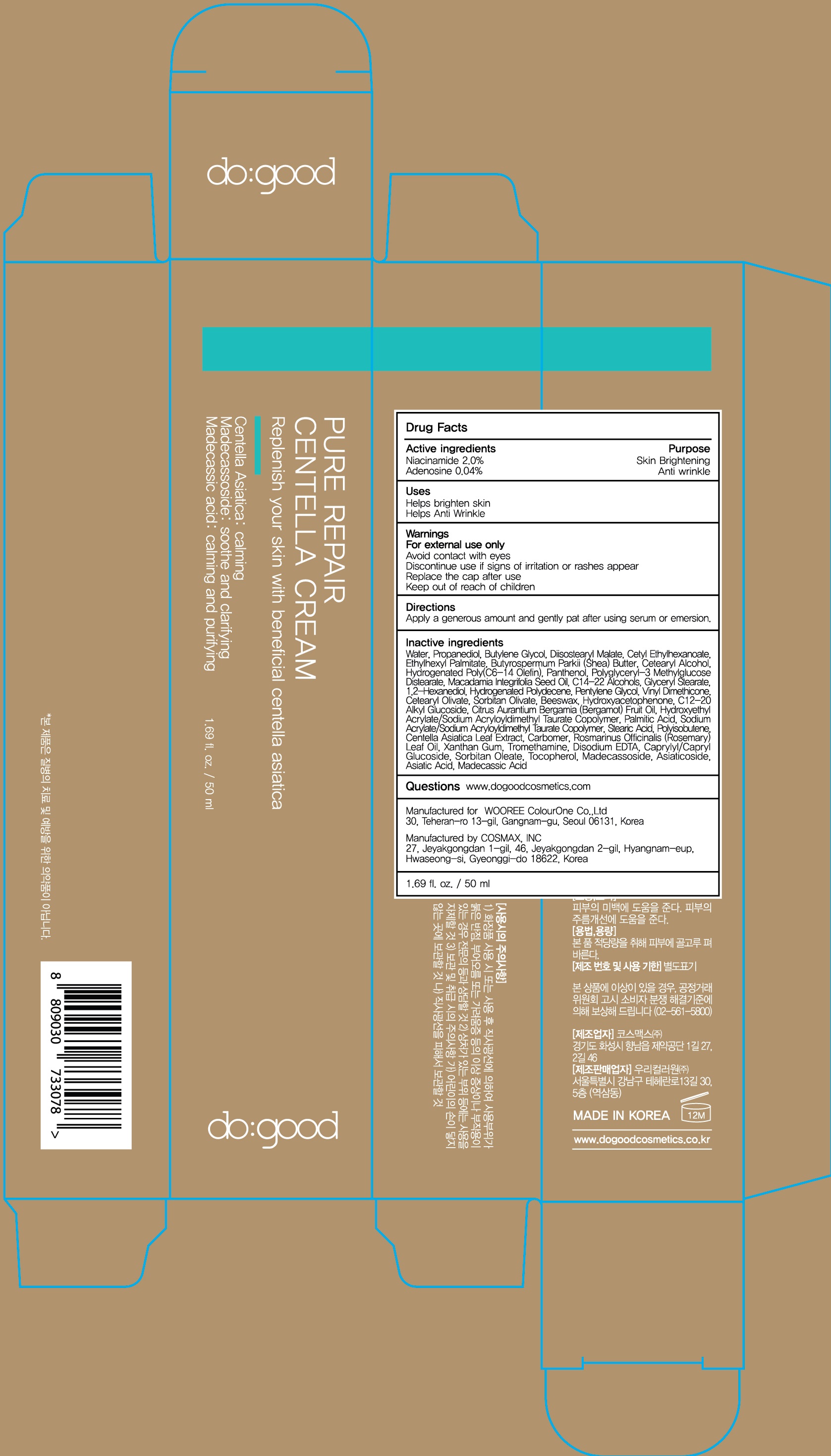 DRUG LABEL: do good Pure Repair Centella
NDC: 72058-040 | Form: CREAM
Manufacturer: WOOREE Colourone Co.,Ltd
Category: otc | Type: HUMAN OTC DRUG LABEL
Date: 20180222

ACTIVE INGREDIENTS: Niacinamide 1.00 g/50 mL; Adenosine 0.02 g/50 mL
INACTIVE INGREDIENTS: Water; Propanediol

ACTIVE INGREDIENT

Active ingredients: Niacinamide 2.0%, Adenosine 0.04%

INACTIVE INGREDIENT

Inactive ingredients:

Water, Propanediol, Butylene Glycol, Diisostearyl Malate, Cetyl Ethylhexanoate, Ethylhexyl Palmitate, Butyrospermum Parkii (Shea) Butter, Cetearyl Alcohol, Hydrogenated Poly(C6-14 Olefin), , Panthenol, Polyglyceryl-3 Methylglucose Distearate, Macadamia Integrifolia Seed Oil, C14-22 Alcohols, Glyceryl Stearate, 1,2-Hexanediol, Hydrogenated Polydecene, Pentylene Glycol, Vinyl Dimethicone, Cetearyl Olivate, Sorbitan Olivate, Beeswax, Hydroxyacetophenone, C12-20 Alkyl Glucoside, Citrus Aurantium Bergamia (Bergamot) Fruit Oil, Hydroxyethyl Acrylate/Sodium Acryloyldimethyl Taurate Copolymer, Palmitic Acid, Sodium Acrylate/Sodium Acryloyldimethyl Taurate Copolymer, Stearic Acid, Polyisobutene, Centella Asiatica Leaf Extract, Carbomer, Rosmarinus Officinalis (Rosemary) Leaf Oil, Xanthan Gum, Tromethamine, Disodium EDTA, Caprylyl/Capryl Glucoside, Sorbitan Oleate, Tocopherol, Madecassoside, Asiaticoside, Asiatic Acid, Madecassic Acid

PURPOSE

Purpose: Skin Brightening, Anti wrinkle

WARNINGS

For external use only.

Avoid contact with eyes.

Discontinue use if signs of irritation or rashes appear.

Replace the cap after use.

Keep out of reach of children

KEEP OUT OF REACH OF CHILDREN

Uses

- Helps brighten skin

- Helps Anti Wrinkle

Directions

Apply a generous amount and gently pat after using serum or emersion.